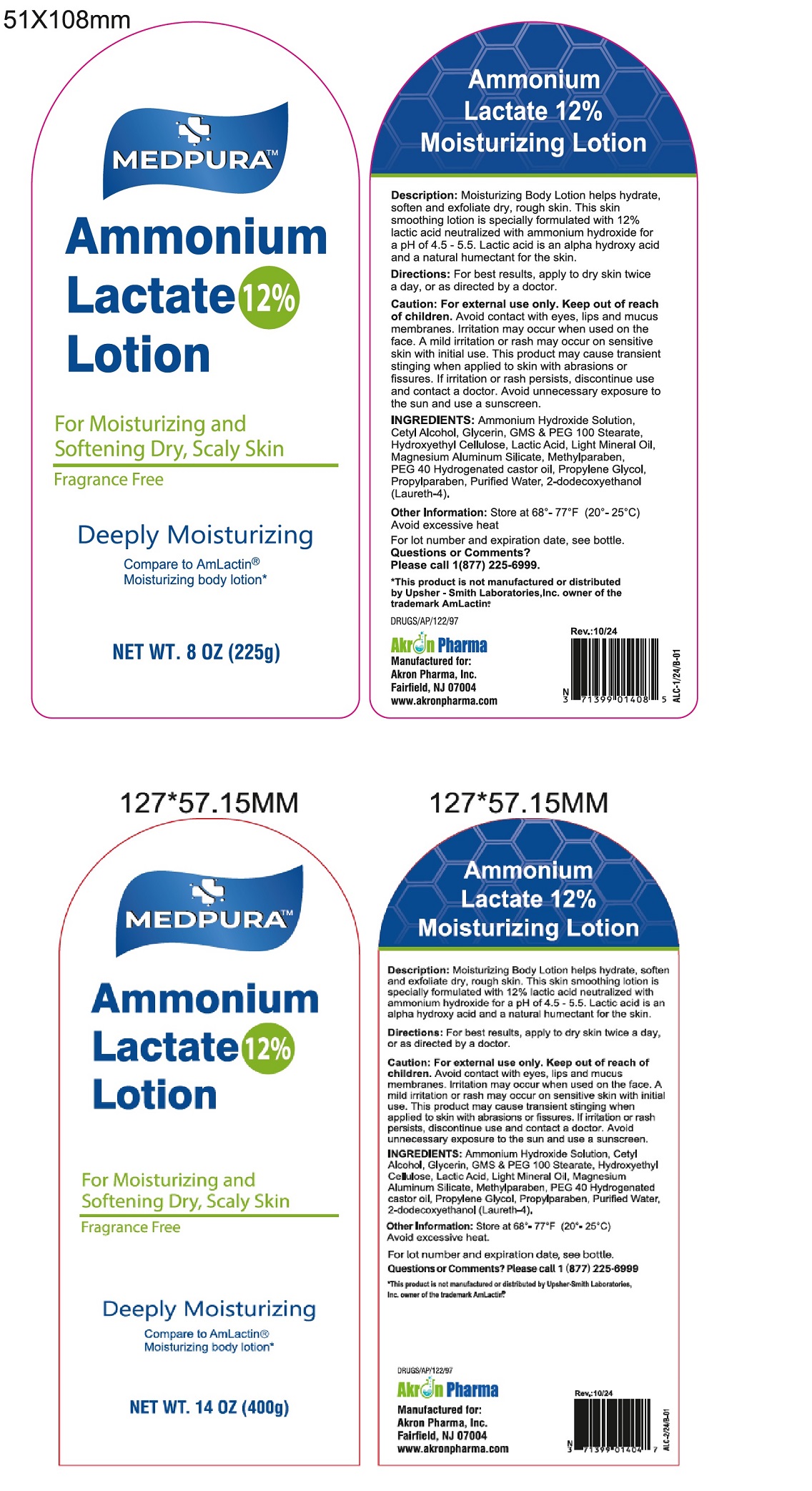 DRUG LABEL: MEDPURA Ammonium Lactate Lotion
NDC: 3713990104085
Manufacturer: Akron Pharma Inc.
Category: other | Type: COSMETIC
Date: 20241201

MEDPURA Ammonium Lactate Lotion 12%
For Moisturizing and Softening Dry, Scaly Skin
Fragrance Free

Description: Ammonium Lactate 12% Moisturizing Lotion helps hydrate, soften and exfoliate dry, rough skin. This skin smoothing cream is specially formulated with 12% lactic acid neutralized with ammonium hydroxide for a pH of 4.5 - 5.5.
Lactic acid is an alpha hydroxy acid and a natural humectant for the skin.
Directions: For best results, apply to dry skin twice a day, or as directed by a doctor.
Caution: For external use only. Keep out of reach of children. Avoid contact with the eyes, lips and mucus membranes. Irritation
may occur when used on the face. If irritation or sensitivity occurs, discontinue use.

Ingredients: Ammonium Hydroxide Solution, Cetyl Alcohol, Glycerin, GMS & PEG 100 Stearate, Hydroxyethyl Cellulose, Lactic Acid,
Light Mineral Oil, Magnesium Aluminum Silicate, Methyl Paraben, PEG 40 Hydrogenated Castor oil, Propylene Glycol, Propyl Paraben, PurifiedWater, 2-dodecoxyethanol (Laureth-4).

Other information: Store at 68°- 77°F (20°- 25°C).
Avoid excessive heat.
For lot number and expiration date, see crimp of the tube
Questions or comments? Please call 1 (877) 225-6999

Manufactured for:

Akron Pharma, Inc.
Fairfield, NJ-07004
www.akronphanna.com